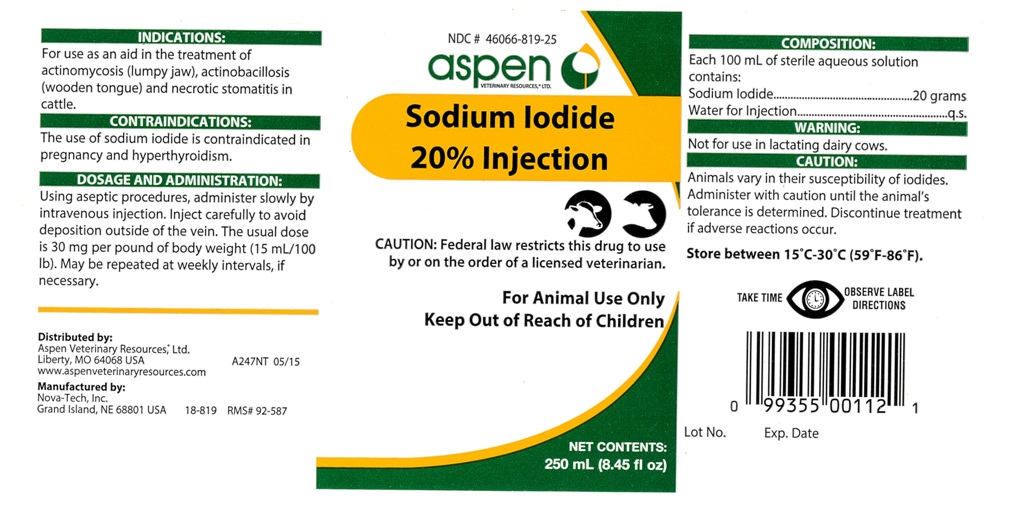 DRUG LABEL: Sodium Iodide 20%
NDC: 46066-819 | Form: INJECTION, SOLUTION
Manufacturer: Aspen Veterinary
Category: animal | Type: PRESCRIPTION ANIMAL DRUG LABEL
Date: 20160127

ACTIVE INGREDIENTS: SODIUM IODIDE 20 g/100 mL

Sodium Iodide 20% Injection

INDICATIONS:

For use as an aid in the treatment of
actinomycosis (lumpy jaw), actinobacillosis
(wooden tongue) and necrotic stomatitis in
cattle.

CONTRAINDICATIONS:

The use of sodium iodide is contraindicated in
pregnancy and hyperthyroidism.

DOSAGE AND ADMINISTRATION:

Using aseptic procedures, administer slowly by
intravenous injection. Inject carefully to avoid
deposition ouside of the vein. The usual dose
is 30 mg per pound of body weight (15 mL/100
lb). May be repeated at weekly intervals, if
necessary.

INFORMATION FOR OWNERS/CAREGIVERS

Distributed by:
Aspen Veterinary Resources, Ltd.
Liberty, MO 64068 USA A247NT 05/15
www.aspenveterinaryresources.com

Manufactrued by:
Nova-Tech, Inc.
Grand Island, NE 68801 USA 18-819 RMS# 92-587

NET CONTENTS:
250 mL (8.45 fl oz)

Lot No. Exp. Date

CAUTION:

Federal law restricts this drug to use
by or on the order of a licensed veterinarian.

VETERINARY INDICATIONS

For Animal Use Only

Keep Out of Reach of Children

COMPOSITION:

Each 100 mL of sterile aqueous solution
contains:
Sodium Iodide..............................20 grams
Water for Injection................................q.s.

WARNING:

Not for use in lactating dairy cows.

CAUTION:

Animals vary in their susceptibility of iodides.
Administer with caution until the animal's
tolerance is determined. Discontinue treatment
if adverse reactions occur.

STORAGE AND HANDLING

Store between 15 degrees C - 30 degrees C (59 degrees F - 86 degrees F).

WARNINGS

TAKE TIME OBSERVE LABEL DIRECTIONS